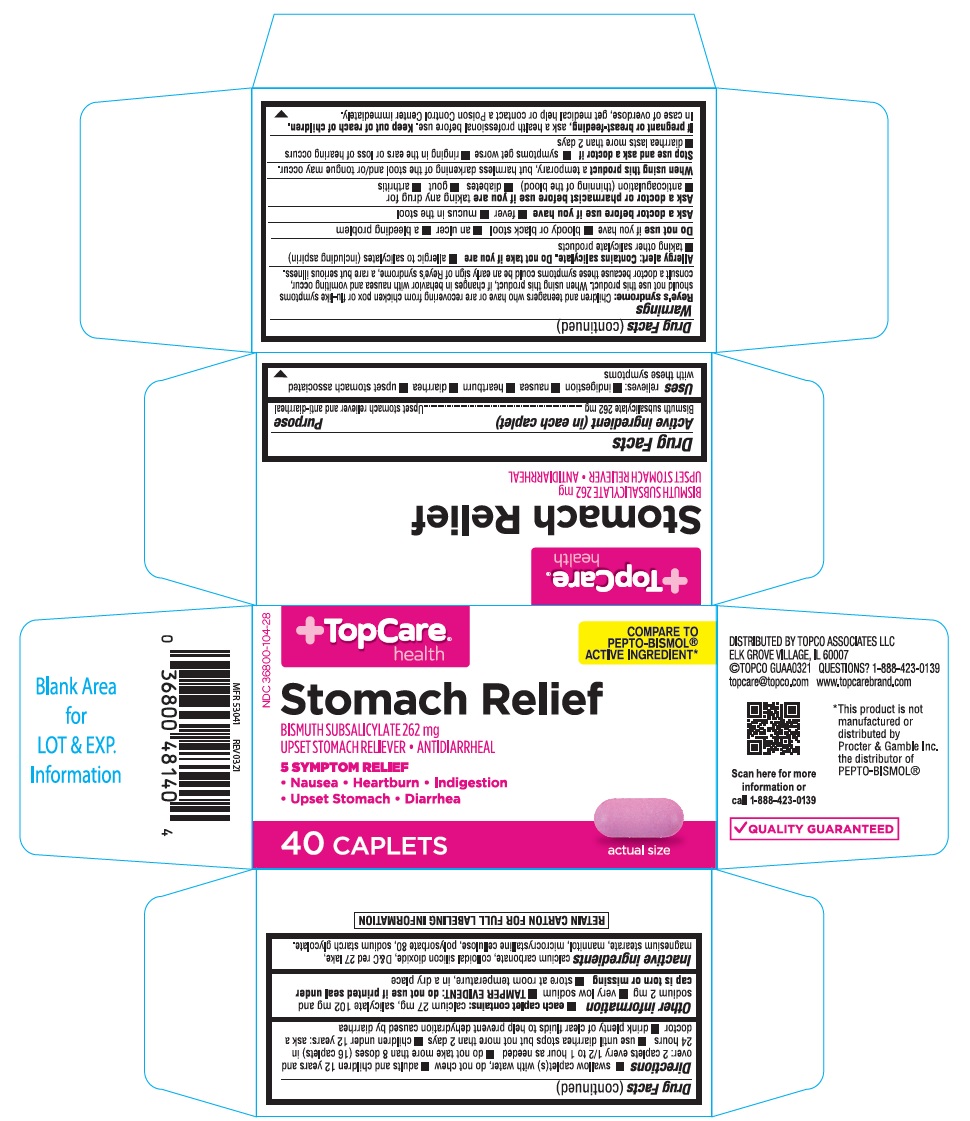 DRUG LABEL: Topco Stomach Relief
NDC: 36800-104 | Form: TABLET
Manufacturer: Topco Associates, LLC
Category: otc | Type: Human OTC Drug Label
Date: 20241226

ACTIVE INGREDIENTS: BISMUTH SUBSALICYLATE 262 mg/1 1
INACTIVE INGREDIENTS: CALCIUM CARBONATE; D&C RED NO. 27; MAGNESIUM STEARATE; MANNITOL; SILICON DIOXIDE; MICROCRYSTALLINE CELLULOSE; POLYSORBATE 80; SODIUM STARCH GLYCOLATE TYPE A POTATO

Topco Stomach Relief Caplets

ACTIVE INGREDIENT(in each caplet)

Bismuth subsalicylate 262 mg

PURPOSE

Upset stomach reliever and anti-diarrheal

USE(S)

relieves:

- indigestion
- nausea
- heartburn
- diarrhea
- upset stomach associated with these symptoms

WARNINGS

Reye's Syndrome: Children and teenagers who have or are recovering from chicken pox or flu-like symptoms should not use this product. When using this product, if changes in behaviour with nausea and vomiting occur, consult a doctor because these symptoms could be an early sign of Reye's Syndrome, a rare but serious illness.

Allergy alert: Contains salicylate. Do not take if you are

- allergic to salicylates (including aspirin)
- taking other salicylate products

DO NOT USE IF YOU HAVE

- bloody or black stool
- an ulcer
- a bleeding problem

ASK A DOCTOR BEFORE USE IF YOU HAVE

- fever
- mucus in the stool

ASK A DOCTOR OR PHARMACIST BEFORE USE IF YOU ARE

taking any drug for

- anticoagulation (thinning of the blood)
- diabetes
- gout
- arthritis

WHEN USING THIS PRODUCT

a temporary, but harmless darkening of the stool and/or tongue may occur

STOP USE AND ASK DOCTOR IF

- symptoms get worse
- ringing in the ears or loss of hearing occurs
- diarrhea lasts more than 2 days

IF PREGNANT OR BREAST-FEEDING,

ask a health professional before use.

KEEP OUT OF REACH OF CHILDREN

In case of overdose, get medical help or contact a Poison Control Center right away.

DIRECTIONS

- swallow caplet(s) with water, do not chew
- adults and children 12 years and over: 2 caplets every 1/2 to 1 hour as needed
- do not take more than 8 doses (16 tablets) in 24 hours
- use until diarrhea stops but not more than 2 days
- children under 12 years: ask a doctor
- drink plenty of clear fluids to help prevent dehydration caused by diarrhea

OTHER INFORMATION

- each caplet contains:
- calcium 27 mg, salicylate 102 mg and sodium 2 mg
- very low sodium
- TAMPER EVIDENT: do not use if printed seal under cap is torn or missing
- store at room temperature, in a dry place

INACTIVE INGREDIENTS

calcium carbonate, colloidal silicon dioxide, D&C red 27 lake, magnesium stearate, mannitol, microcrystalline cellulose, polysorbate 80, sodium starch glycolate.

PRINCIPAL DISPLAY PANEL

Topcare health

COMPATE TO PEPTO-BISMOL® ACTIVE INGREDIENT*

NDC 36800-104-28

Stomach Relief
BISMUTH SUBSALICYLATE 262 mg
UPSET STOMACH RELIEVER / ANTIDIARRHEAL
5 SYMPTOM RELIEF

- Nausea
- Heartburn
- Indigestion
- Upset stomach
- Diarrhea

40 CAPLETS